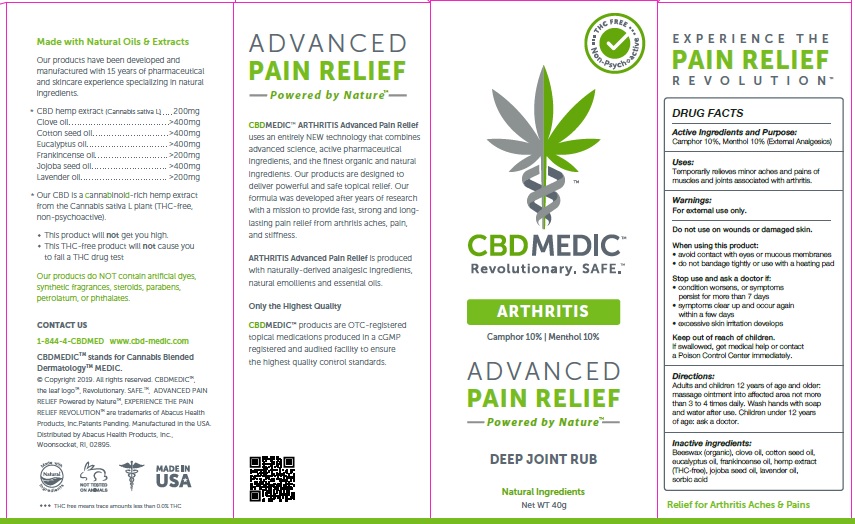 DRUG LABEL: CBDMEDIC Arthritis Pain Relief
NDC: 24909-733 | Form: OINTMENT
Manufacturer: AIDANCE SKINCARE & TOPICAL SOLUTIONS, LLC
Category: otc | Type: HUMAN OTC DRUG LABEL
Date: 20190306

ACTIVE INGREDIENTS: CAMPHOR (SYNTHETIC) 100 mg/1 g; MENTHOL 100 mg/1 g
INACTIVE INGREDIENTS: WHITE WAX; CLOVE OIL; COTTONSEED OIL; EUCALYPTUS OIL; FRANKINCENSE OIL; HEMP; JOJOBA OIL; LAVENDER OIL; SORBIC ACID

CBDMEDIC Arthritis Pain Relief

Active Ingredients and Purpose

Camphor 10%, Menthol 10% (External Analgesics)

Uses

Temporarily relieves minor aches and pains of muscles and joints associated with arthritis.

Warnings

For external use only. Do not use on wounds or damaged skin. When using this product: • avoid contact with eyes or mucous membranes • do not bandage tightly or use with a heating pad. Stop use and ask a doctor if: • condition worsens, or symptoms persist for more than 7 days • symptoms clear up and occur again within a few days • excessive skin irritation develops.

Keep out of reach of children

If swallowed, get medical help or contact a Poison Control Center immediately.

Directions

Adults and children 12 years of age and older: massage ointment into affected area not more than 3 to 4 times daily. Wash hands with soap and water after use. Children under 12 years of age: ask a doctor.

Inactive ingredients

Beeswax (organic), clove oil, cotton seed oil, eucalyptus oil, frankincense oil, hemp extract (THC-free), jojoba seed oil, lavender oil, sorbic acid